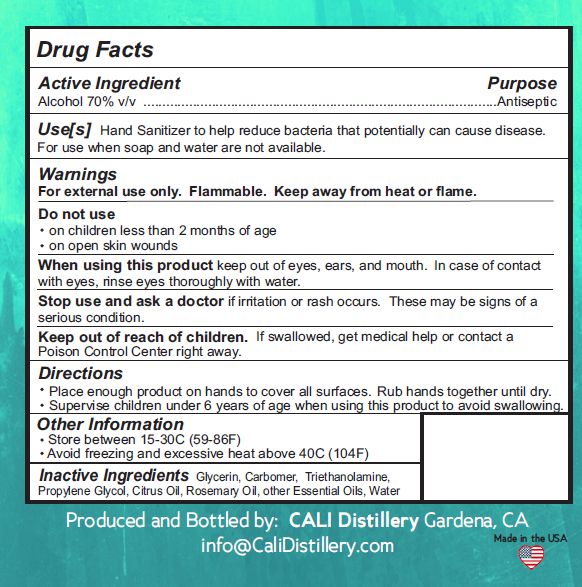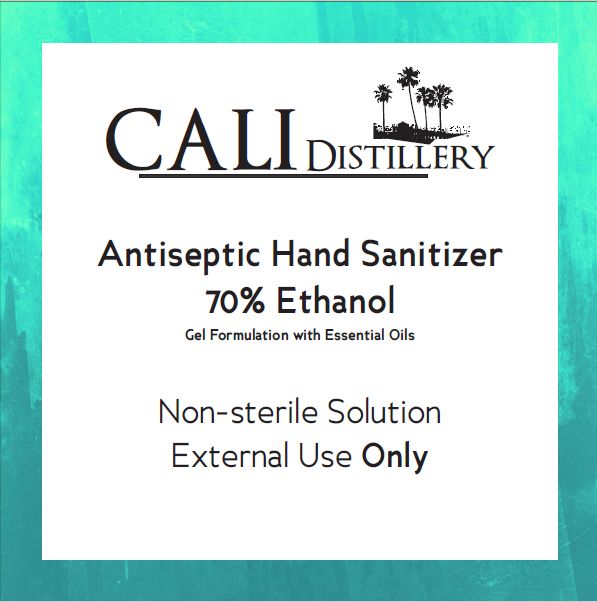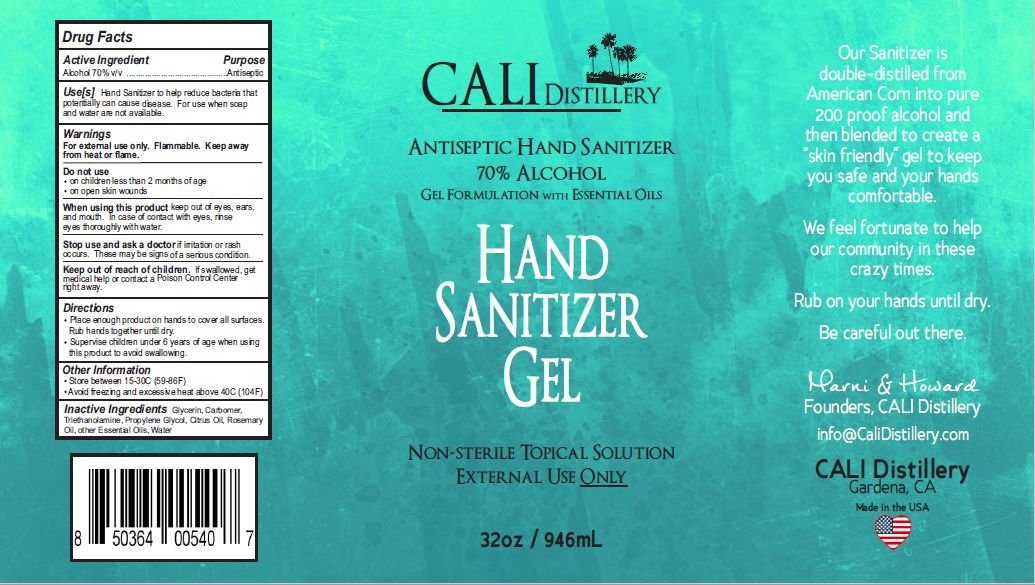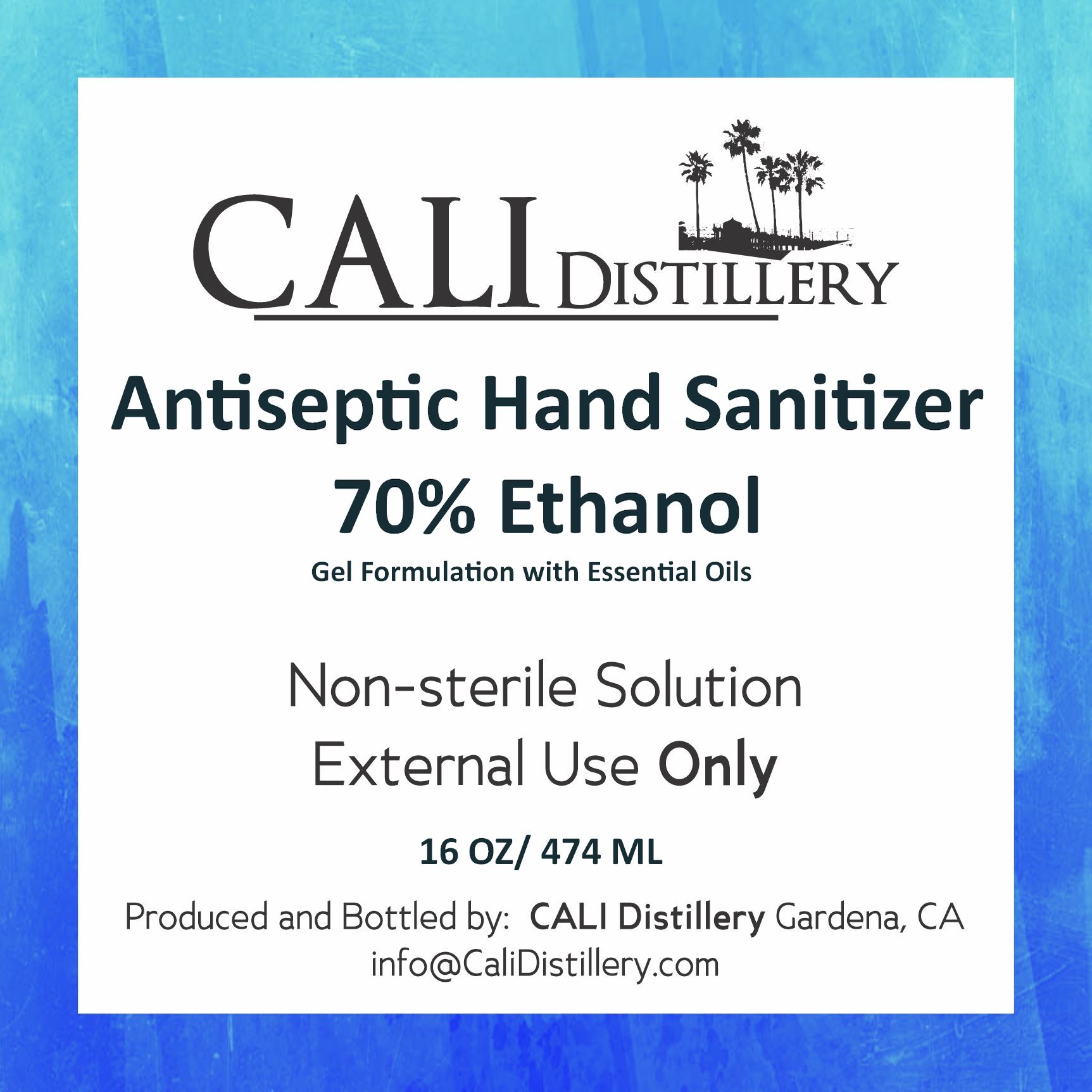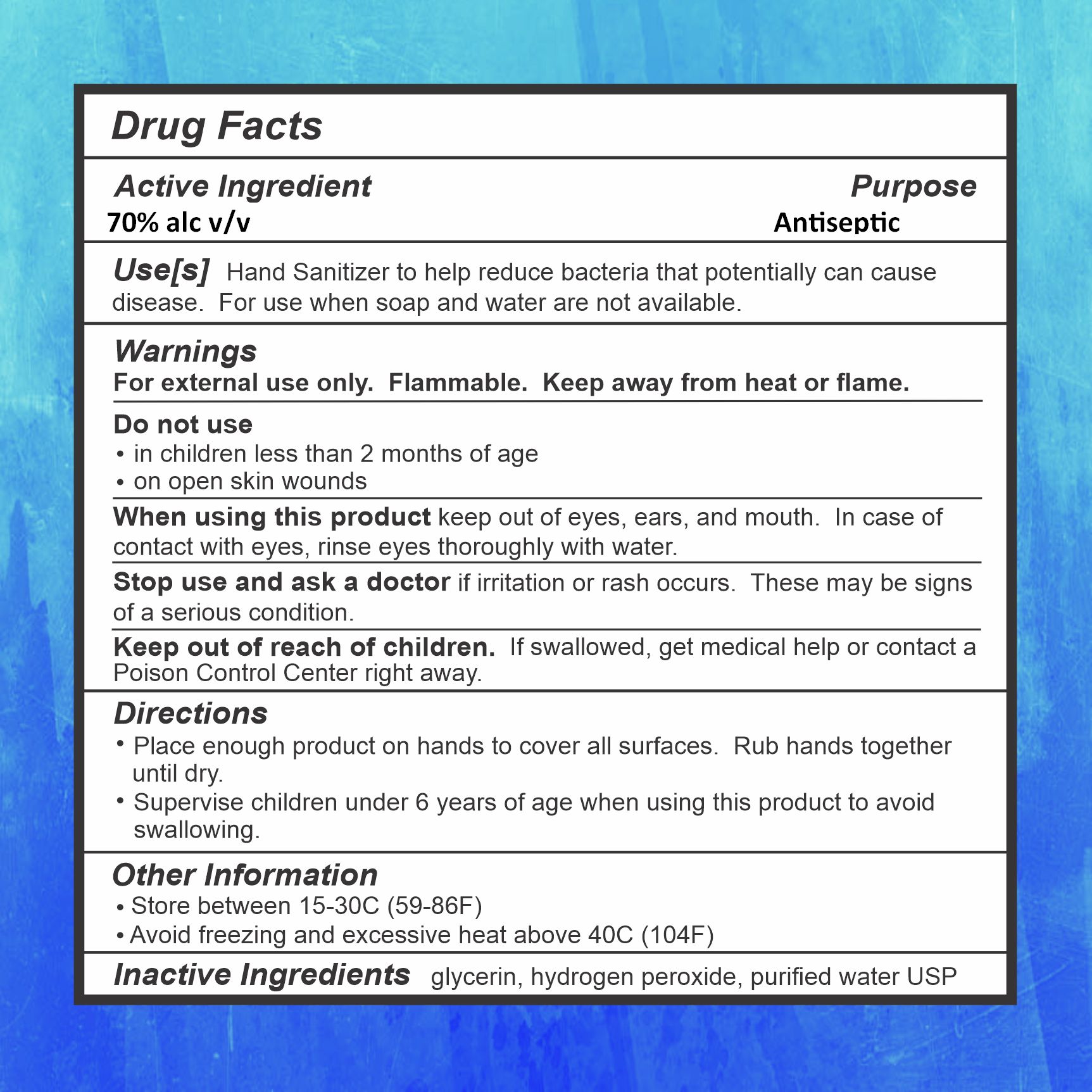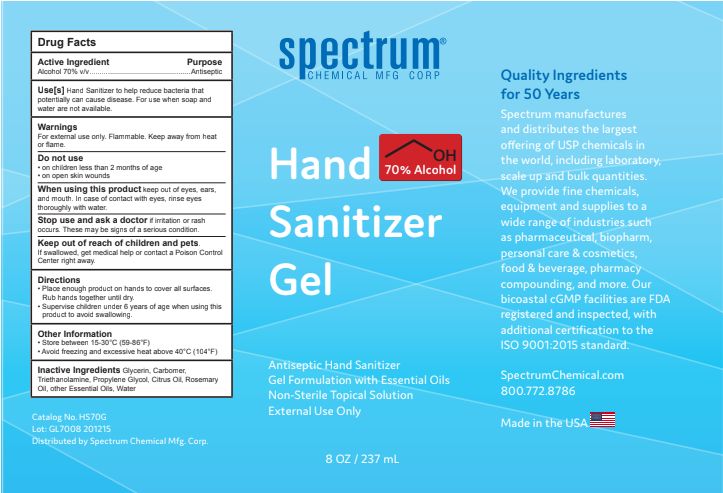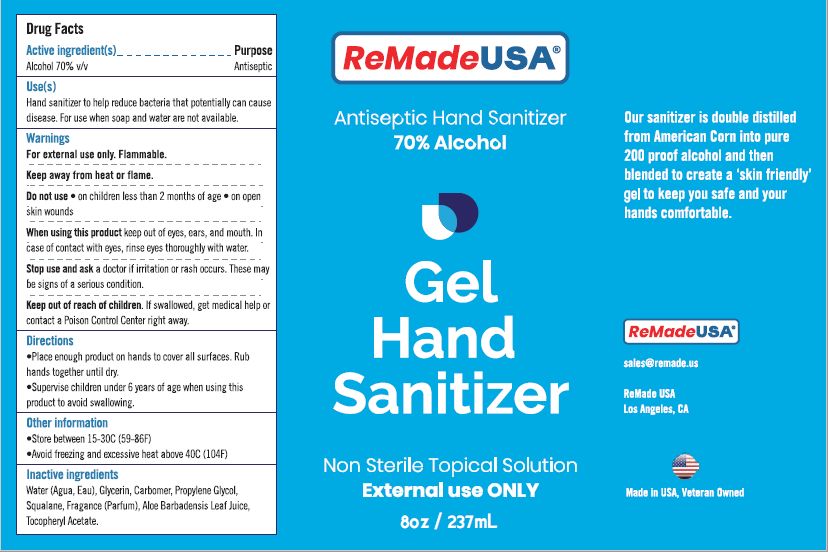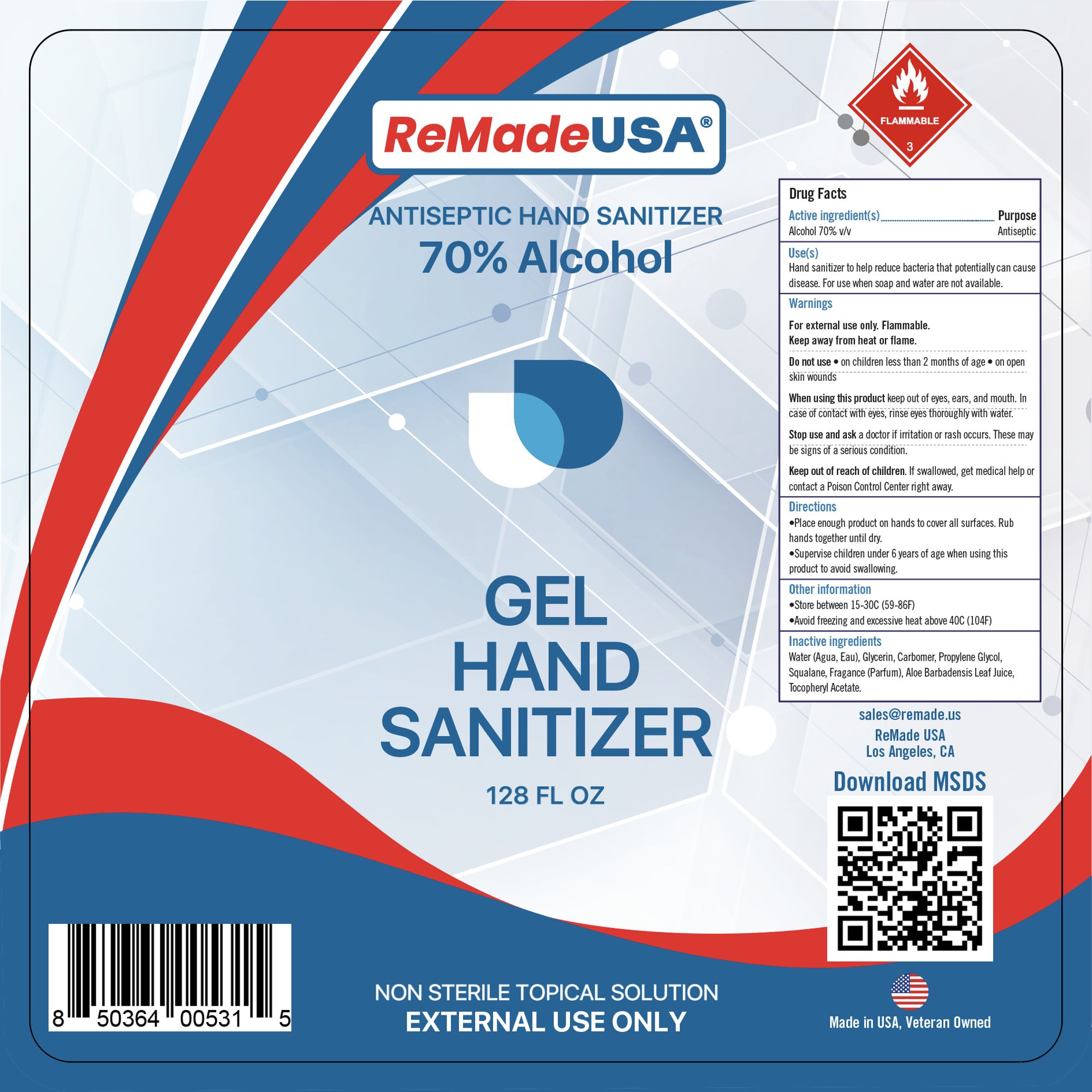 DRUG LABEL: Cali Distillery Gel Hand Sanitizer
NDC: 74500-0004 | Form: GEL
Manufacturer: CALI Distillery
Category: otc | Type: HUMAN OTC DRUG LABEL
Date: 20220113

ACTIVE INGREDIENTS: ALCOHOL 70 mL/100 mL
INACTIVE INGREDIENTS: PROPYLENE GLYCOL 2 mL/100 mL; TROLAMINE 0.1 mL/100 mL; CARBOMER 940 0.5 mL/100 mL; GLYCERIN 1.45 mL/100 mL; WATER

The hand sanitizer is manufactured using only the following United States Pharmacopoeia (USP) grade ingredients in the preparation of the product (percentage in final product formulation) consistent with World Health Organization (WHO) recommendations:

1. Alcohol (ethanol) (USP or Food Chemical Codex (FCC) grade) (70 to 72%, volume/volume (v/v)) in an aqueous solution denatured according to Alcohol and Tobacco Tax and Trade Bureau regulations in 27 CFR part 20.
2. Glycerol (1.45% v/v).
3. Carbomer
4. 85% triethanolamine
5. Propylene glycol
6. Sterile distilled water or boiled cold water.

Active Ingredient(s)

Alcohol 70% v/v. Purpose: Antiseptic

Purpose

Antiseptic, Hand Sanitizer

Use

Hand Sanitizer to help reduce bacteria that potentially can cause disease. For use when soap and water are not available.

Warnings

For external use only. Flammable. Keep away from heat or flame

Do not use

- on children less than 2 months of age
- on open skin wounds

When using this product keep out of eyes, ears, and mouth. In case of contact with eyes, rinse eyes thoroughly with water.
Stop use and ask a doctor if irritation or rash occurs. These may be signs of a serious condition.
Keep out of reach of children. If swallowed, get medical help or contact a Poison Control Center right away.

Stop use and ask a doctor if irritation or rash occurs. These may be signs of a serious condition.

Keep out of reach of children. If swallowed, get medical help or contact a Poison Control Center right away.

Directions

- Place enough product on hands to cover all surfaces. Rub hands together until dry.
- Supervise children under 6 years of age when using this product to avoid swallowing.

Other information

- Store between 15-30C (59-86F)
- Avoid freezing and excessive heat above 40C (104F)

Inactive ingredients

glycerin, carbomer to gel, triethanolamine for PH balance, Propylene Glycol, Citrus oil, purified water USP

Package Label - Principal Display Panel

474 mL NDC: 74500-0004-1 front label

474 mL NDC: 74500-0004-1 back label

1 gallon NDC: 74500-0004-5 front label

32 oz label

gallon NDC: 74500-0004-5 back label

remade 8 ounce